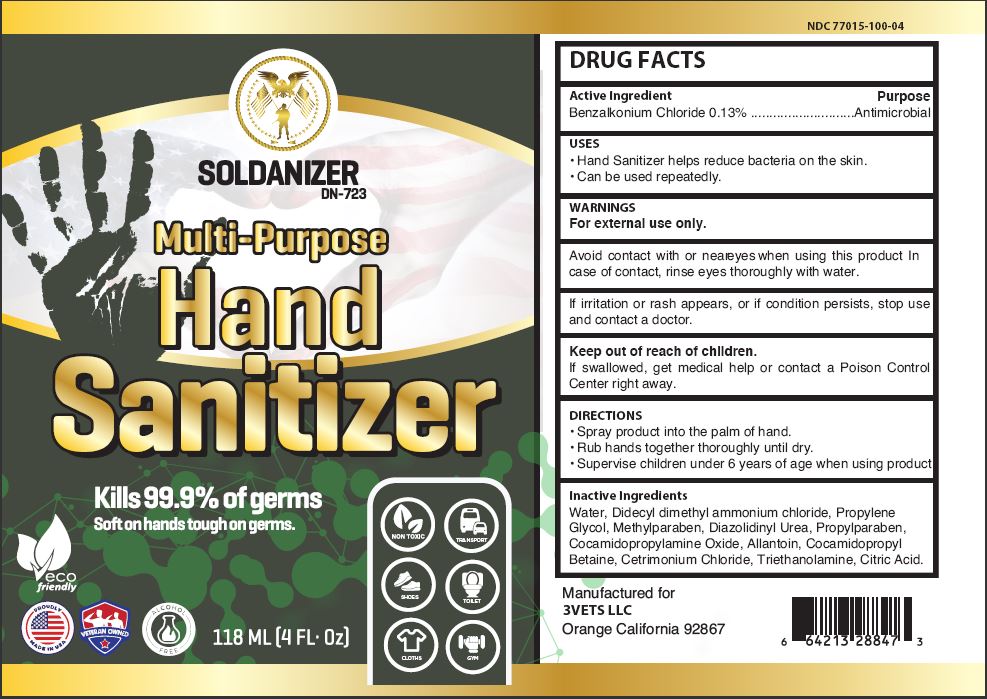 DRUG LABEL: SOLDANIZER

NDC: 77015-100 | Form: SPRAY
Manufacturer: 3VETS LLC
Category: otc | Type: HUMAN OTC DRUG LABEL
Date: 20230110

ACTIVE INGREDIENTS: BENZALKONIUM CHLORIDE 0.13 g/100 mL
INACTIVE INGREDIENTS: WATER; DIDECYLDIMONIUM CHLORIDE; PROPYLENE GLYCOL; METHYLPARABEN; DIAZOLIDINYL UREA; PROPYLPARABEN; COCAMIDOPROPYLAMINE OXIDE; ALLANTOIN; COCAMIDOPROPYL BETAINE; CETRIMONIUM CHLORIDE; TROLAMINE; ANHYDROUS CITRIC ACID

3VETS LLC - SOLDANIZER DN-723, MULTI-PURPOSE HAND SANITIZER (77015-100)

ACTIVE INGREDIENT

BENZALKONIUM CHLORIDE 0.13%

PURPOSE

ANTIMICROBIAL

USES

- HAND SANITIZER HELPS REDUCE BACTERIA ON THE SKIN.
- CAN BE USED REPEATEDLY.

WARNINGS

FOR EXTERNAL USE ONLY.

AVOID CONTACT WITH OR NEAR EYES WHEN USING THIS PRODUCT. IN CASE OF CONTACT, RINSE EYES THOROUGHLY WITH WATER.

IF IRRITATION OR RASH APPEARS, OR IF CONDITION PERSISTS, STOP USE AND CONTACT A DOCTOR.

KEEP OUT OF REACH OF CHILDREN.

IF SWALLOWED, GET MEDICAL HELP OR CONTACT A POISON CONTROL CENTER RIGHT AWAY.

DIRECTIONS

- SPRAY PRODUCT INTO THE PALM OF HAND.
- RUB HANDS TOGETHER THOROUGHLY UNTIL DRY.
- SUPERVISE CHILDREN UNDER 6 YEARS OF AGE WHEN USING PRODUCT.

INACTIVE INGREDIENTS

WATER, DIDECYL DIMETHYL AMMONIUM CHLORIDE, PROPYLENE GLYCOL, METHYLPARABEN, DIAZOLIDINYL UREA, PROPYLPARABEN, COCAMIDOPROPYLAMINE OXIDE, ALLANTOIN, COCAMIDOPROPYL BETAINE, CETRIMONIUM CHLORIDE, TRIETHANOLAMINE, CITRIC ACID.